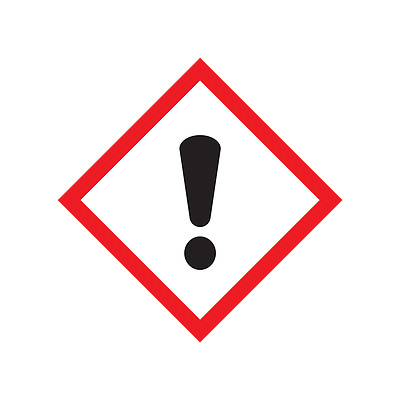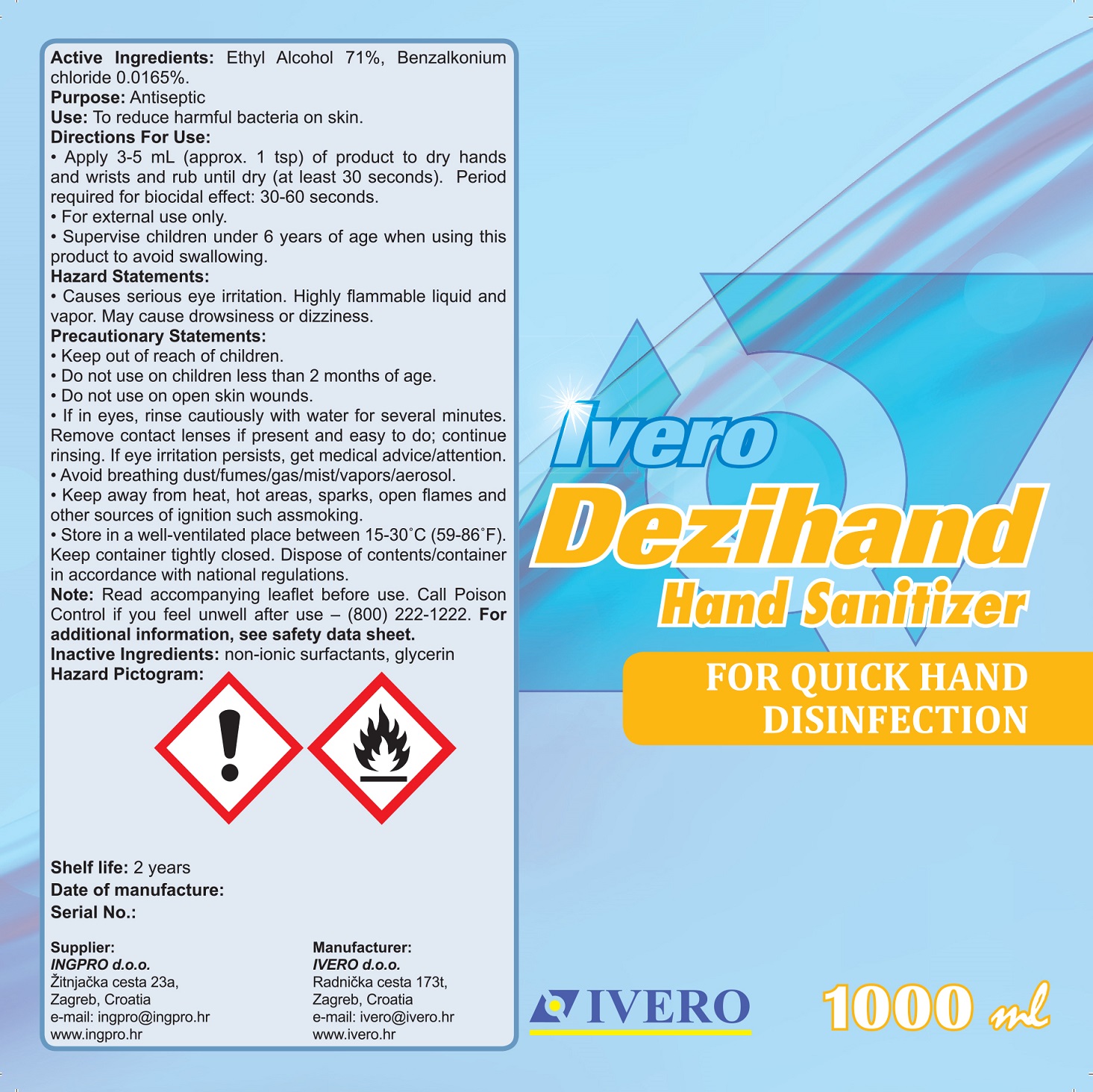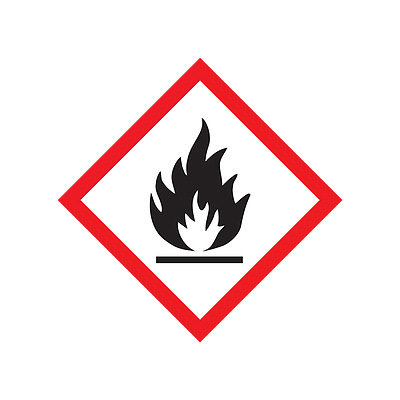 DRUG LABEL: Dezihand Hand Sanitizer
NDC: 80133-002 | Form: GEL
Manufacturer: IVERO d.o.o.
Category: otc | Type: HUMAN OTC DRUG LABEL
Date: 20200909

ACTIVE INGREDIENTS: BENZALKONIUM CHLORIDE 0.0165 g/100 mL; ALCOHOL 71 mL/100 mL
INACTIVE INGREDIENTS: GLYCERIN

Active Ingredients

Ethyl Alcohol 71% v/v

Benzalkonium chloride 0.0165% v/v

Purpose

Antiseptic

Use

To reduce harmful bacteria on skin.

Directions For Use

- Apply 3-5mL (approx. 1 tsp) of product to dry hands and wrists and rub until dry (at least 30 seconds). Period required for biocidal effect: 30-60 seconds.
- For external use only.
- Supervise children under 6 years of age when using product to avoid swallowing.

Hazard Statements

- Causes serious eye irritation. Highly flammable liquid and vapor. May cause drowsiness or dizziness.

Precautionary Statements

- Keep out of reach of children.
- Do not use on children less than 2 months of age.
- Do not use on open skin wounds.
- If in eyes, rinse cautiously with water for several minutes. Remove contact lenses if present and easy to do; continue rinsing. If eye irritation persists, get medical advice/attention.
- Avoid breathing dust/fumes/gas/mist/vapors/aerosol.
- Keep away from heat, hot areas, sparks, open flames and other sources of ignition such as smoking.
- Store in a well-ventilated place between 15-30°C (59-86°F). Keep container tightly closed. Dispose of contents/container in accordance with national regulations.

- Keep out of reach of children.

Note

Read accompanying leaflet before use. Call Poison Control if you feel unwell after use - (800) 222-1222. For additional information, see safety data sheet.

Inactive Ingredients

non-ionic surfactants, glycerin

Package Label - Principal Display Panel

1000mL NDC: 80133-002-10